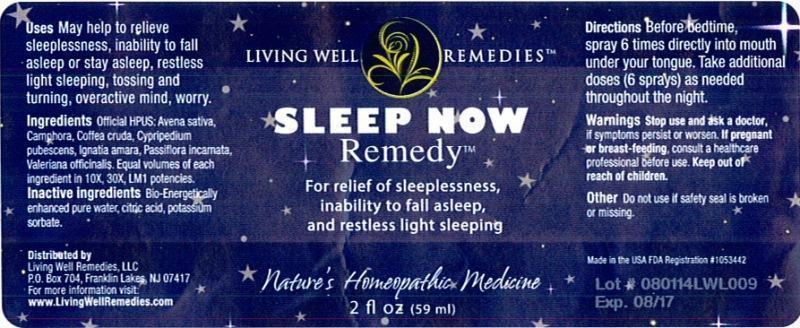 DRUG LABEL: Sleep Now Remedy
NDC: 53852-0009 | Form: LIQUID
Manufacturer: Living Well Remedies, LLC
Category: homeopathic | Type: HUMAN OTC DRUG LABEL
Date: 20141030

ACTIVE INGREDIENTS: AVENA SATIVA FLOWERING TOP 10 [hp_X]/59 mL; CAMPHOR (NATURAL) 10 [hp_X]/59 mL; ARABICA COFFEE BEAN 10 [hp_X]/59 mL; CYPRIPEDIUM PARVIFOLUM ROOT 10 [hp_X]/59 mL; STRYCHNOS IGNATII SEED 10 [hp_X]/59 mL; PASSIFLORA INCARNATA FLOWERING TOP 10 [hp_X]/59 mL; VALERIAN 10 [hp_X]/59 mL
INACTIVE INGREDIENTS: WATER; CITRIC ACID MONOHYDRATE; POTASSIUM SORBATE

Sleep Now Remedy

DOSAGE AND ADMINISTRATION

Directions: Before bedtime, spray 6 times directly into mouth under your tongue. Take additional doses (6 sprays) as needed throughout the night.

WARNINGS

Warnings: Stop use and ask a doctor, if symptoms persist or worsen. If pregnant or breast-feeding, consult a healthcare professional before use.

Keep out of reach of children.

OTHER SAFETY INFORMATION

Other: Do not use if safety seal is broken or missing.

PURPOSE

Uses: Before bedtime, spray 6 times directly into mouth under your tongue. Take additional doses (6 sprays) as needed throughout the night.

ACTIVE INGREDIENT

Ingredients: Official HPUS: Avena sativa, Camphora, Coffea cruda, Cypripedium pubescens, Ignatia amara, Passiflora incarnata, Valeriana officinalis. Equal volumes of each ingredient in 10X, 30X, LM1 potencies.

INACTIVE INGREDIENT

Inactive ingredients: Bio-Energetically enhanced pure water, citric acid, potassium sorbate.

INDICATIONS AND USAGE

Uses: Before bedtime, spray 6 times directly into mouth under your tongue.

Take additional doses (6 sprays) as needed throughout the night.